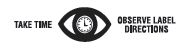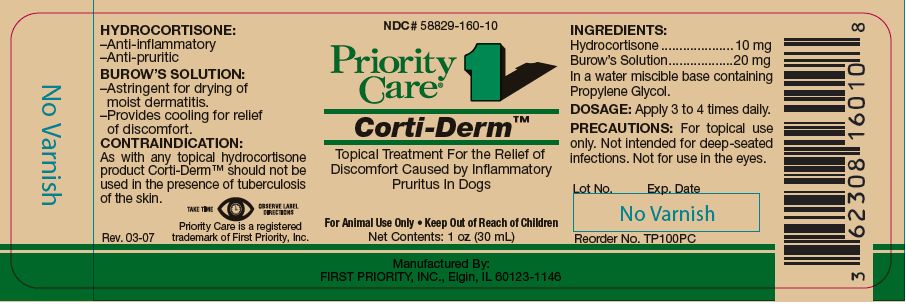 DRUG LABEL: Corti Derm
NDC: 58829-160 | Form: SOLUTION
Manufacturer: FIRST PRIORITY INCORPORATED
Category: animal | Type: OTC ANIMAL DRUG LABEL
Date: 20221115

ACTIVE INGREDIENTS: HYDROCORTISONE 10.2 mg/1 mL; ALUMINUM ACETATE .73 mg/1 mL; ACETIC ACID 0.624 mg/1 mL

Corti-Derm™

INFORMATION FOR OWNERS/CAREGIVERS

Topical Treatment For the Relief of Discomfort Caused by Inflammatory Pruritus In Dogs

For Animal Use Only • Keep Out of Reach of Children

HYDROCORTISONE:

− Anti-inflammatory

− Anti-pruritic

BURROW'S SOLUTION:

− Astringent for drying of moist dermatitis.

− Provides cooling for relief of discomfort.

CONTRAINDICATION:

As with any topical hydrocortisone product Cort-Derm™ should not be used in the presence of tuberculosis of the skin.

INGREDIENTS:

Hydrocortisone........................... 10 mg

Burow's Solution......................... 20 mg

INACTIVE INGREDIENT

In a water miscible base containing Propylene Glycol.

DOSAGE:

Apply 3 to 4 times daily.

PRECAUTIONS:

For topical use only. Not intented for deep-seated infections. Not for use in the eyes.

Net Contents:

1 oz (30 mL) Reorder No. TP100PC

4 oz (120 mL) Reorder No. TP102PC

NOT RETURNABLE IF OUTDATED

Made in U.S.A.

Manufactured By: First Priority, Inc., Elgin, IL U.S.A.

www.prioritycare.com

1 oz (30 mL) Bottle/Case Label

Rev. 03-07